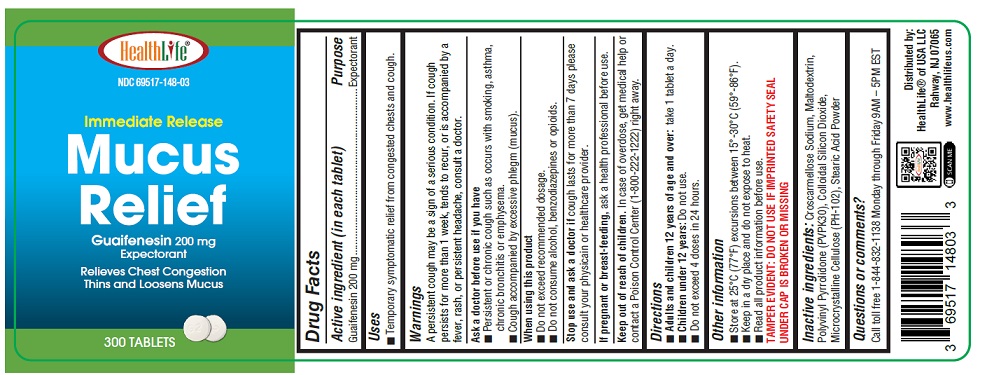 DRUG LABEL: Guaifenesin 200mg
NDC: 69517-148 | Form: TABLET
Manufacturer: HEALTHLIFE OF USA LLC
Category: otc | Type: HUMAN OTC DRUG LABEL
Date: 20250822

ACTIVE INGREDIENTS: GUAIFENESIN 200 mg/1 1
INACTIVE INGREDIENTS: CROSCARMELLOSE SODIUM; MALTODEXTRIN; POVIDONE K30; SILICON DIOXIDE; CELLULOSE, MICROCRYSTALLINE; STEARIC ACID

Active ingredient (in each tablet)

Guaifenesin 200 mg

Purpose

Expectorant

Uses

- Temporary symptomatic relief from congested chests and cough.

Warnings

A persistent cough may be a sign of a serious condition. If cough persists for more than 1 week, tends to recur, or is accompanied by a fever, rash, or persistent headache, consult a doctor.

Ask a doctor before use if you have

- Persistent or chronic cough such as occurs with smoking, asthma, chronic bronchitis, or emphysema
- Cough accompanied by too much phlegm (mucus)

When using this product

- Do not exceed recommended dosage.
- Do not consume alcohol, benzodiazepines or opioids.

Stop use and ask a doctor ifcough lasts for more than 7 days please consult your physicain or healthcare provider.

If pregnant or breast-feeding,

ask a health professional before use.

Keep out of reach of children.

In case of overdose, get medical help or contact a Poison Control Center (1-800-222-1222) right away.

Directions

- Adults and children 12 years of age and over:take 1 tablet a day.
- Children under 12 years:Do not use.
- Do not exceed 4 doses in 24 hours.

Other Information

- Store at 25°C (77°F) excursions between 15°-30°C (59°-86°F).
- Keep in a dry place and do not expose to heat.
- Read all product information before use.
- TAMPER EVIDENT: DO NOT USE IF IMPRINTED SAFETY SEAL UNDER CAP IS BROKEN OR MISSING

Inactive Ingredients

Croscarmellose Sodium, Maltodextrin, Polyvinyl Pyrrolidone (PVPK30), Colloidal Silicon Dioxide, Microcrystalline Cellulose (PH-102), Stearic Acid Powder

Questions or comments?

Call toll free 1-844-832-1138 Monday through Friday 9AM – 5PM EST